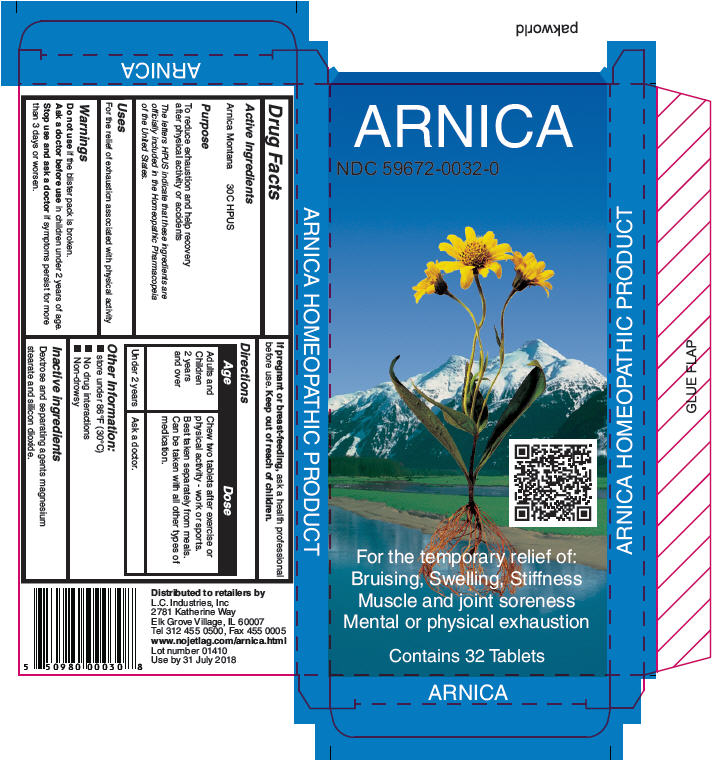 DRUG LABEL: Arnica
NDC: 59672-0032 | Form: TABLET
Manufacturer: LC Industries
Category: homeopathic | Type: HUMAN OTC DRUG LABEL
Date: 20140707

ACTIVE INGREDIENTS: Arnica Montana 30 [hp_C]/1 1
INACTIVE INGREDIENTS: Dextrose 248 mg/1 1; Silicon Dioxide; Magnesium stearate

Arnica

Drug Facts

Active Ingredients

Arnica Montana 30C HPUS

Purpose

To reduce exhaustion and help recovery after physical activity or accidents

The letters HPUS indicate that these ingredients are officially included in the Homeopathic Pharmacopeia of the United States.

Uses

For the relief of exhaustion associated with physical activity

Warnings

Do not use if the blister pack is broken.

Ask a doctor before use in children under 2 years of age.

Stop use and ask a doctor if symptoms persist for more than 3 days or worsen.

PREGNANCY OR BREAST FEEDING

If pregnant or breast-feeding, ask a health professional before use.

Keep out of reach of children.

Directions

Age | Dose
Adults and Children 2 years and over | Chew two tablets after exercise or physical activity - work or sports. Best taken separately from meals. Can be taken with all other types of medication.
Under 2 years | Ask a doctor.

Other Information

- store under 86°F (30°C)
- No drug interactions
- Non-drowsy

Inactive ingredients

Dextrose and separating agents magnesium stearate and silicon dioxide.

Distributed to retailers by
L.C. Industries, Inc
2781 Katherine Way
Elk Grove Village, IL 60007

PRINCIPAL DISPLAY PANEL - 32 Tablet Blister Pack Box

ARNICA

NDC 59672-0032-0

For the temporary relief of:
Bruising, Swelling, Stiffness
Muscle and joint soreness
Mental or physical exhaustion

Contains 32 Tablets